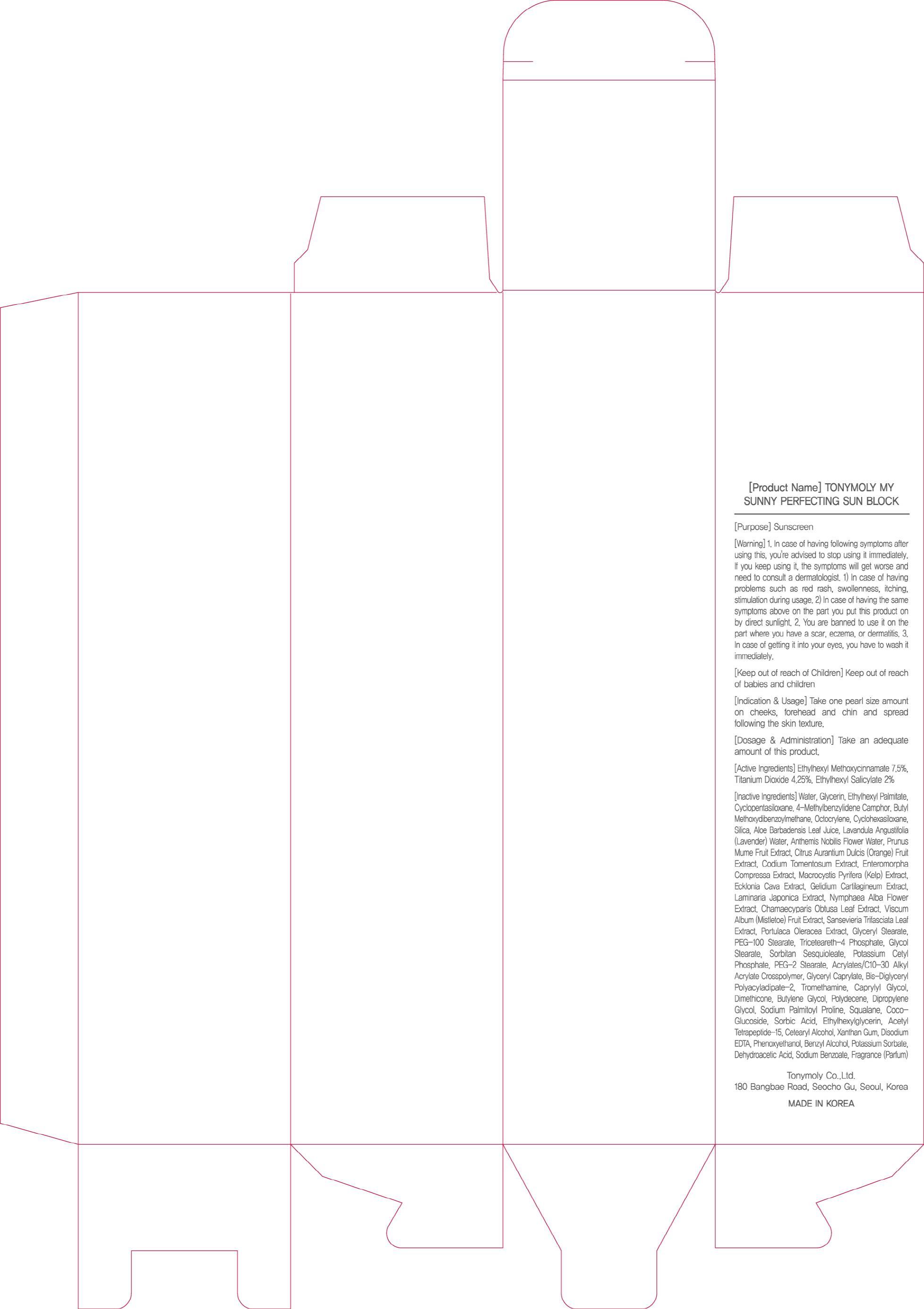 DRUG LABEL: TONYMOLY My Sunny Perfecting Sun Block
NDC: 59078-047 | Form: CREAM
Manufacturer: TONYMOLY CO., LTD.
Category: otc | Type: HUMAN OTC DRUG LABEL
Date: 20140626

ACTIVE INGREDIENTS: OCTINOXATE 7.5 mg/100 mL; TITANIUM DIOXIDE 4.25 mg/100 mL; OCTISALATE 2 mg/100 mL
INACTIVE INGREDIENTS: Water; Glycerin

ACTIVE INGREDIENT

Active Ingredients: Ethylhexyl Methoxycinnamate 7.5%, Titanium Dioxide 4.25%, Ethylhexyl Salicylate 2%

INACTIVE INGREDIENT

Inactive Ingredients:
Water, Glycerin, Ethylhexyl Palmitate, Cyclopentasiloxane, 4-Methylbenzylidene Camphor, Butyl Methoxydibenzoylmethane, Octocrylene, Cyclohexasiloxane, Silica, Aloe Barbadensis Leaf Juice, Lavandula Angustifolia (Lavender) Water, Anthemis Nobilis Flower Water, Prunus Mume Fruit Extract, Citrus Aurantium Dulcis (Orange) Fruit Extract, Codium Tomentosum Extract, Enteromorpha Compressa Extract, Macrocystis Pyrifera (Kelp) Extract, Ecklonia Cava Extract, Gelidium Cartilagineum Extract, Laminaria Japonica Extract, Nymphaea Alba Flower Extract, Chamaecyparis Obtusa Leaf Extract, Viscum Album (Mistletoe) Fruit Extract, Sansevieria Trifasciata Leaf Extract, Portulaca Oleracea Extract, Glyceryl Stearate, PEG-100 Stearate, Triceteareth-4 Phosphate, Glycol Stearate, Sorbitan Sesquioleate, Potassium Cetyl Phosphate, PEG-2 Stearate, Acrylates/C10-30 Alkyl Acrylate Crosspolymer, Glyceryl Caprylate, Bis-Diglyceryl Polyacyladipate-2, Tromethamine, Caprylyl Glycol, Dimethicone, Butylene Glycol, Polydecene, Dipropylene Glycol, Sodium Palmitoyl Proline, Squalane, Coco-Glucoside, Sorbic Acid, Ethylhexylglycerin, Acetyl Tetrapeptide-15, Cetearyl Alcohol, Xanthan Gum, Disodium EDTA, Phenoxyethanol, Benzyl Alcohol, Potassium Sorbate, Dehydroacetic Acid, Sodium Benzoate, Fragrance(Parfum)

PURPOSE

Purpose: Sunscreen

WARNINGS

Warning:
1. In case of having following symptoms after using this, you're advised to stop using it immediately. If you keep using it, the symptoms will get worse and need to consult a dermatologist.
1) In case of having problems such as red rash, swollenness, itching, stimulation during usage.
2) In case of having the same symptoms above on the part you put this product on by direct sunlight.
2. You are banned to use it on the part where you have a scar, eczema, or dermatitis.
3. In case of getting it into your eyes, you have to wash it immediately.

KEEP OUT OF REACH OF CHILDREN

Keep out of reach of babies and children

INDICATIONS AND USAGE

Take one pearl size amount on cheeks, forehead and chin and spread following the skin texture.

DOSAGE AND ADMINISTRATION

Take an adequate amount of this product.